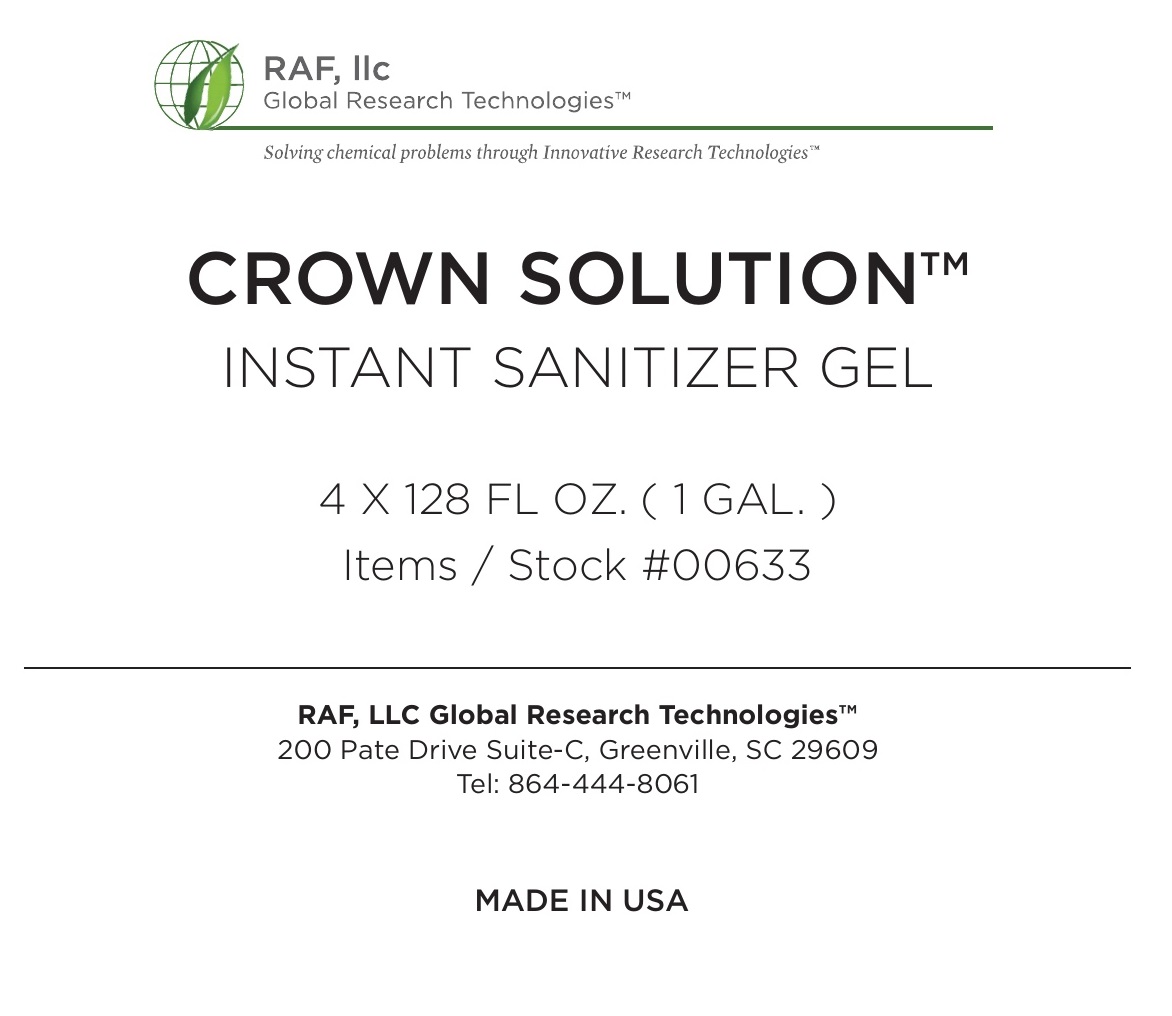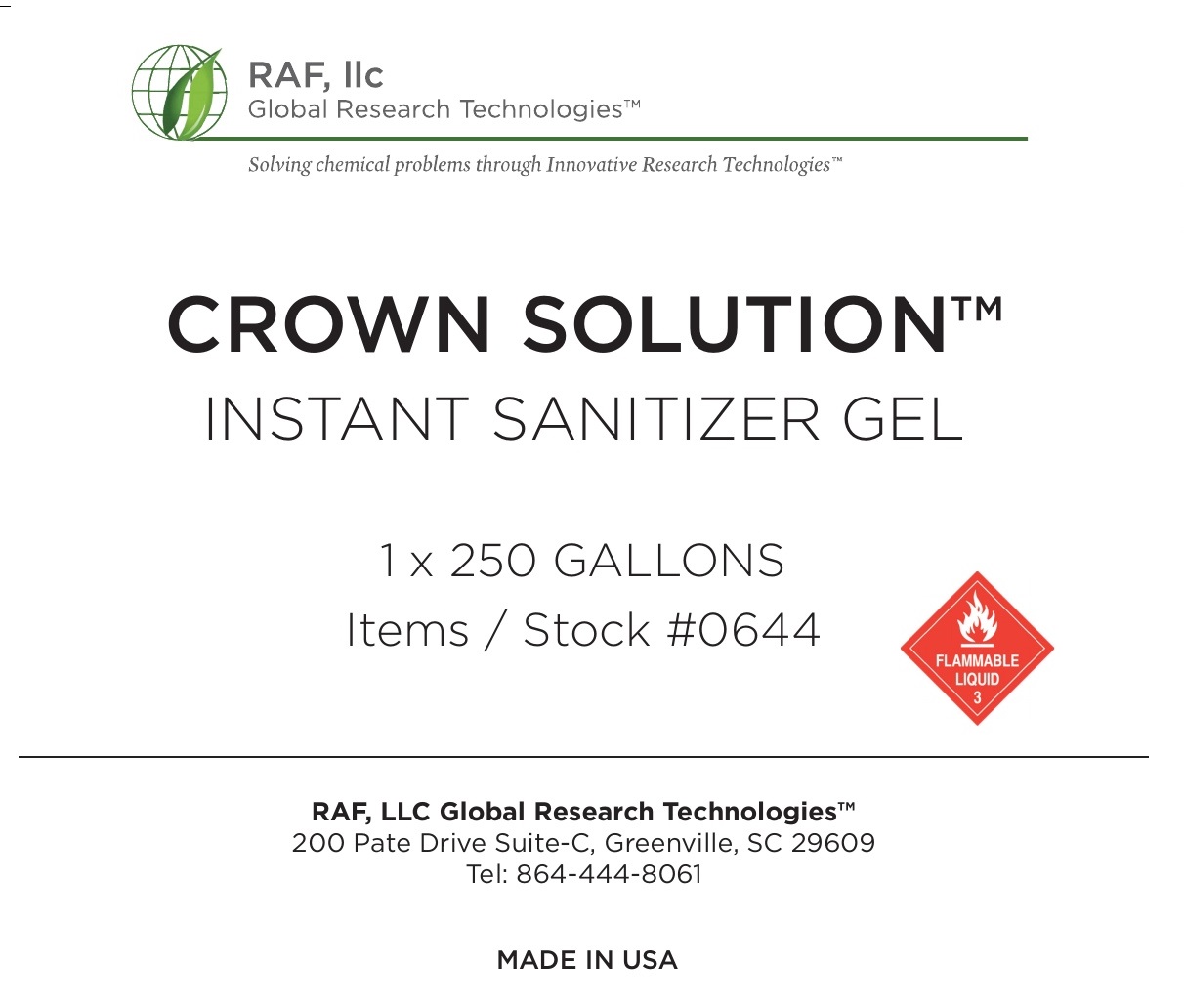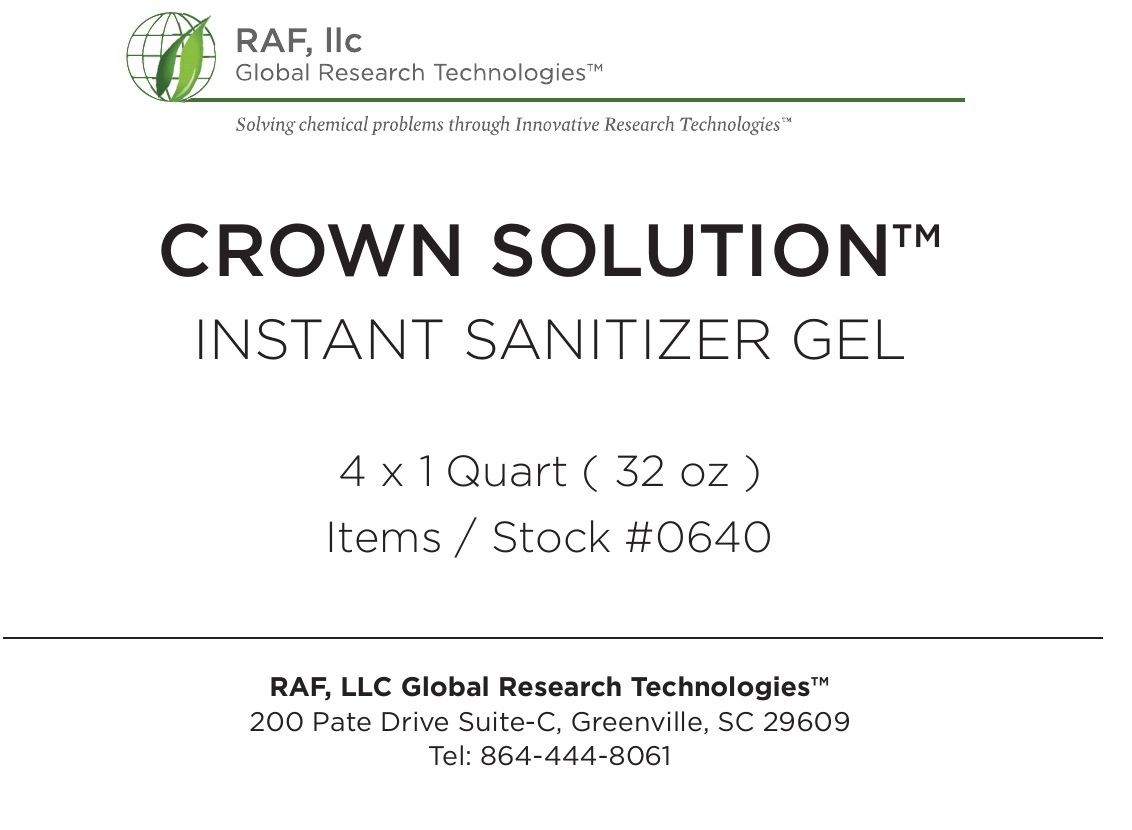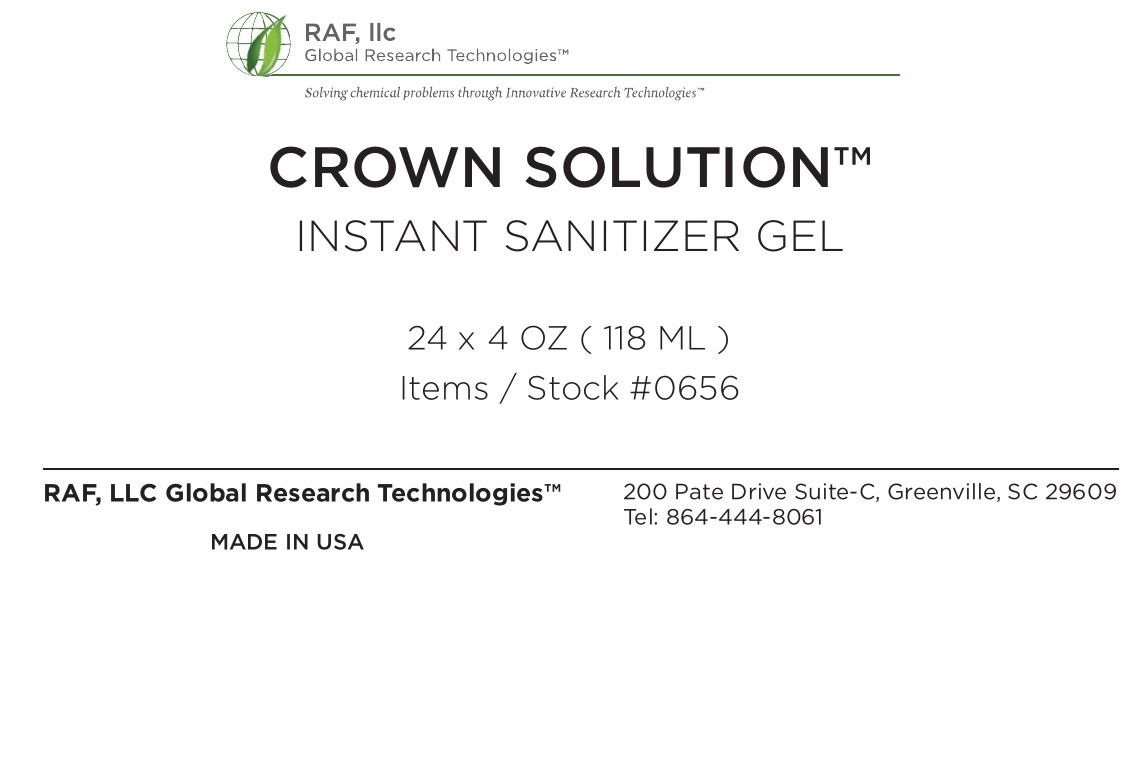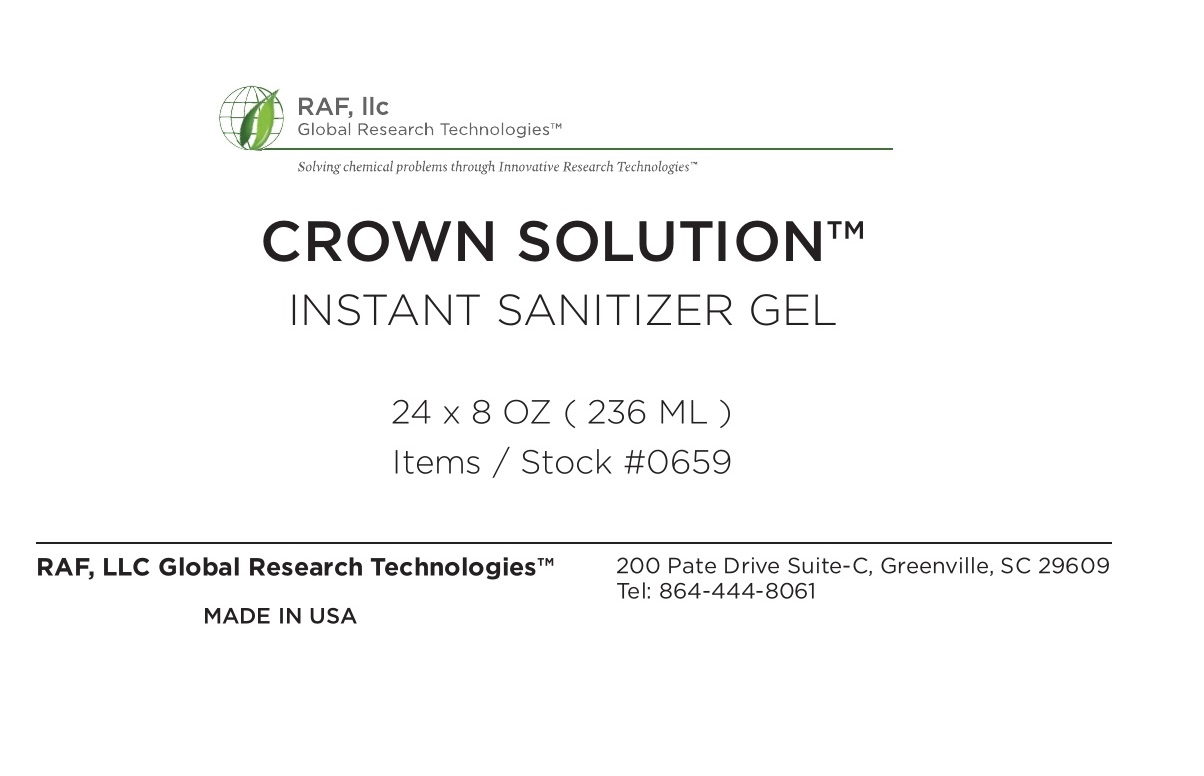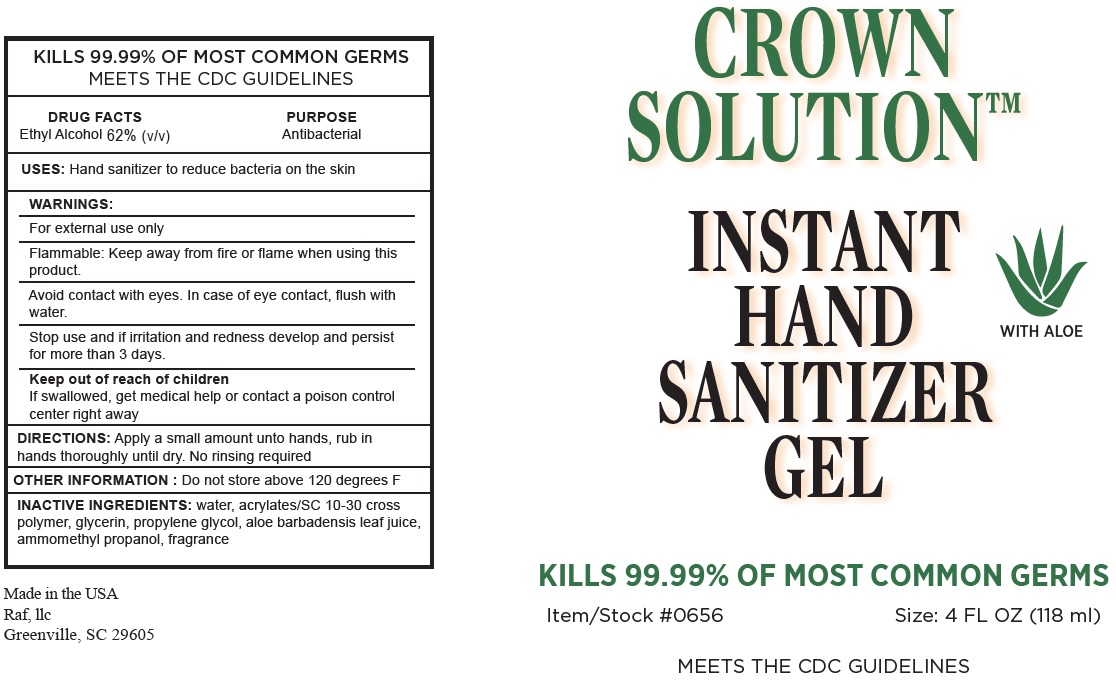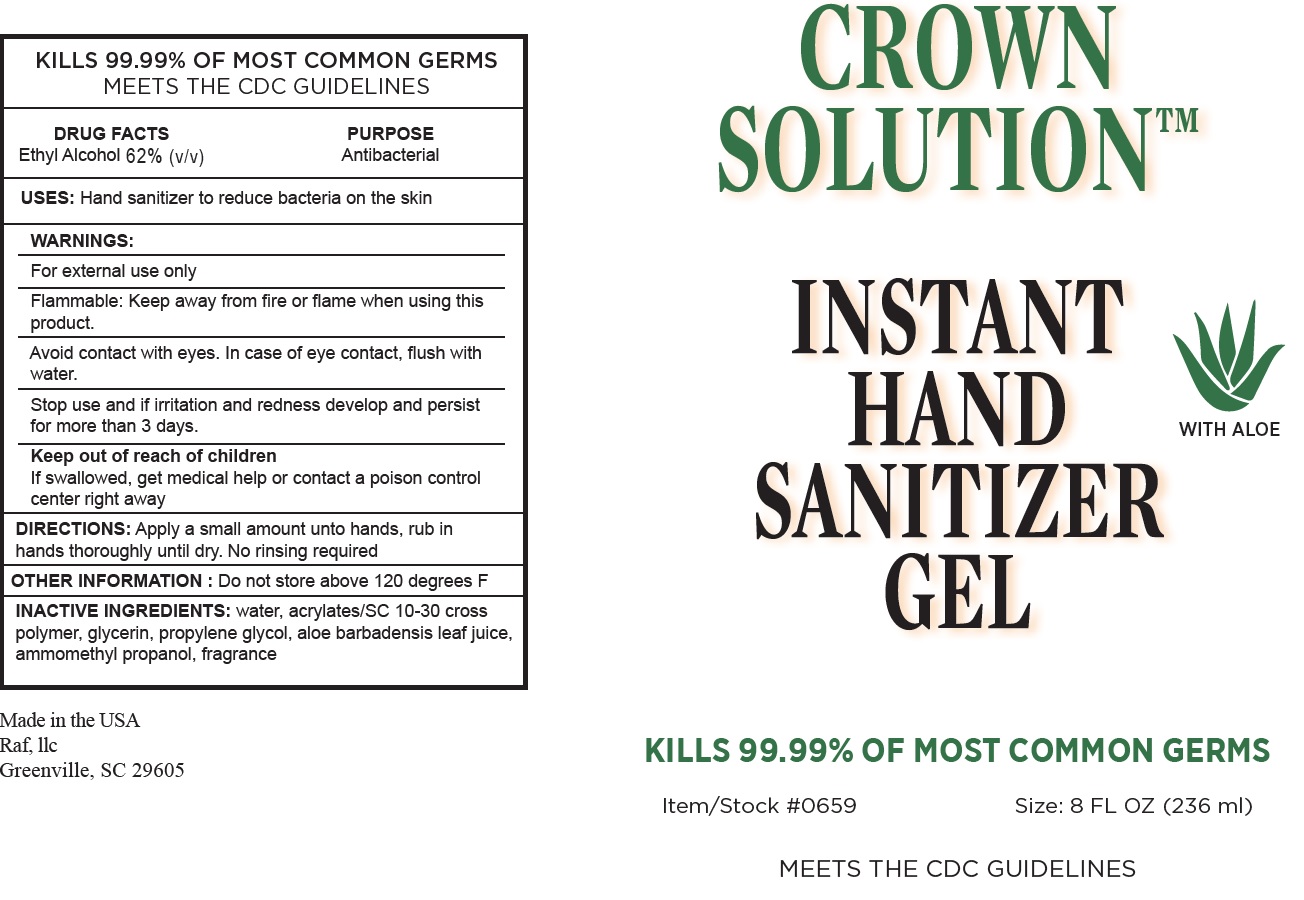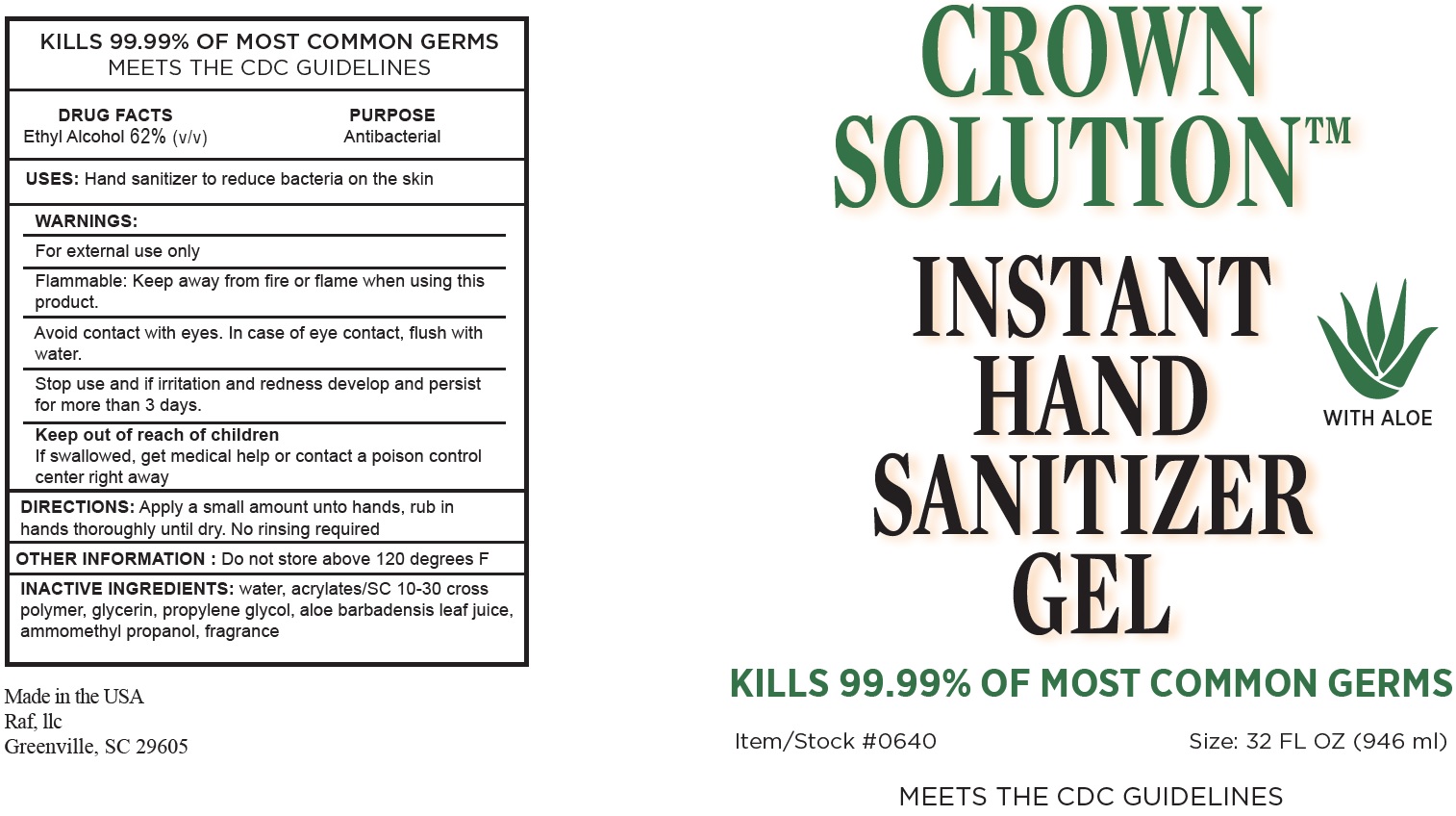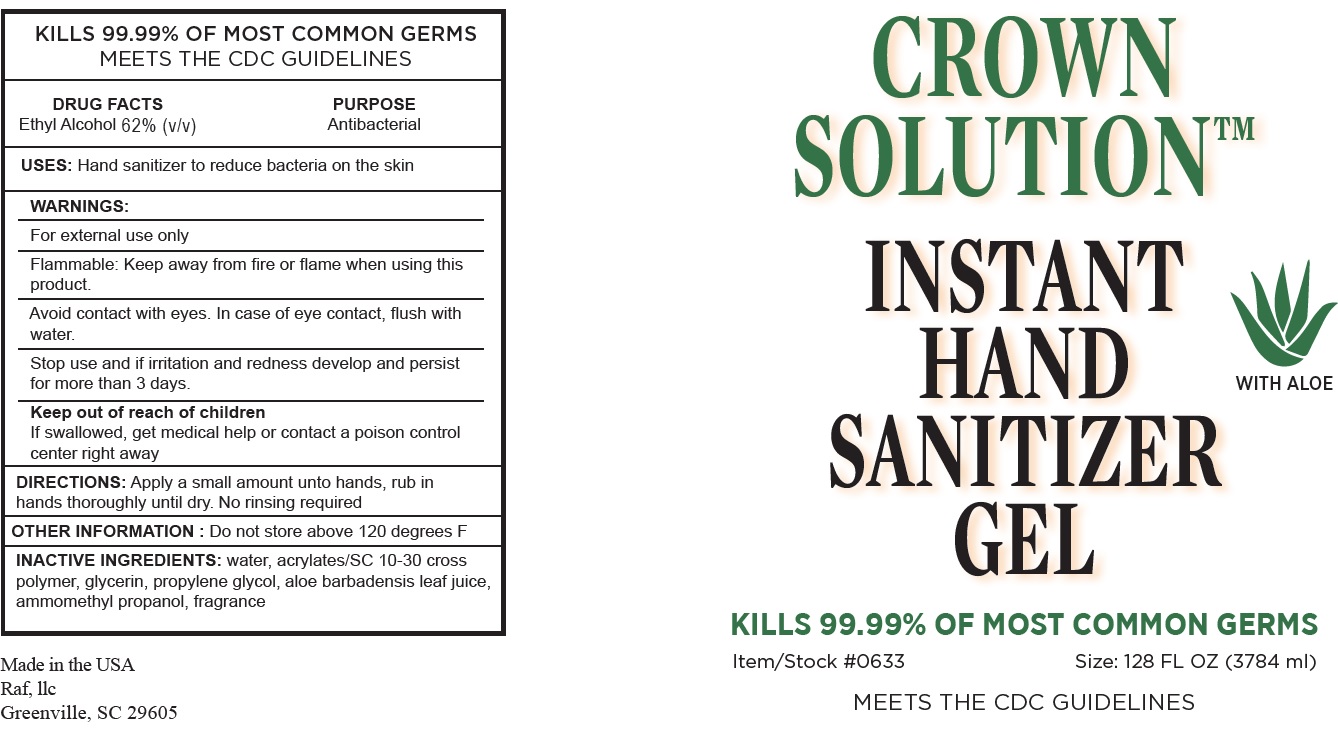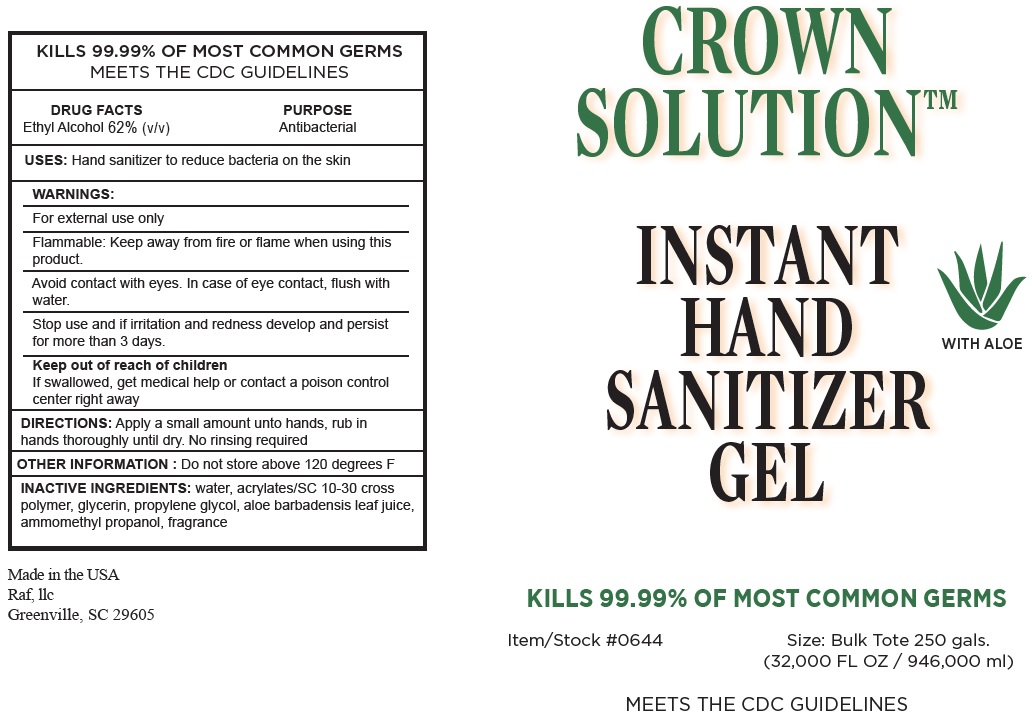 DRUG LABEL: Crown Solutions Instant Hand Sanitizer Gel
NDC: 81570-001 | Form: GEL
Manufacturer: RAF, LLC
Category: otc | Type: HUMAN OTC DRUG LABEL
Date: 20210914

ACTIVE INGREDIENTS: ALCOHOL 62 mL/100 mL
INACTIVE INGREDIENTS: WATER; GLYCERIN; PROPYLENE GLYCOL; ALOE VERA LEAF; AMINOMETHYLPROPANOL

Crown Solutions Instant Hand Sanitizer Gel

ACTIVE INGREDIENT

Ethyl Alcohol 62% (v/v)

PURPOSE

Antibacterial

USES:

Hand sanitizer to reduce bacteria on the skin

WARNINGS:

For external use only

Flammable: Keep away from fire or flame

when using this product.

Avoid contact with eyes. In case of eye contact, flush with water.

Stop use and if

irritation and redness develop and persist for more than 3 days.

Keep out of reach of children

If swallowed, get medical help or contact a poison control center right away

DIRECTIONS:

Apply a small amount unto hands, rub in hands thoroughly until dry. No rinsing required

OTHER INFORMATION :

Do not store above 120 degrees F

INACTIVE INGREDIENTS:

water, acrylates/SC 10-30 cross polymer, glycerin, propylene glycol, aloe barbadensis leaf juice, ammomethyl propanol, fragrance